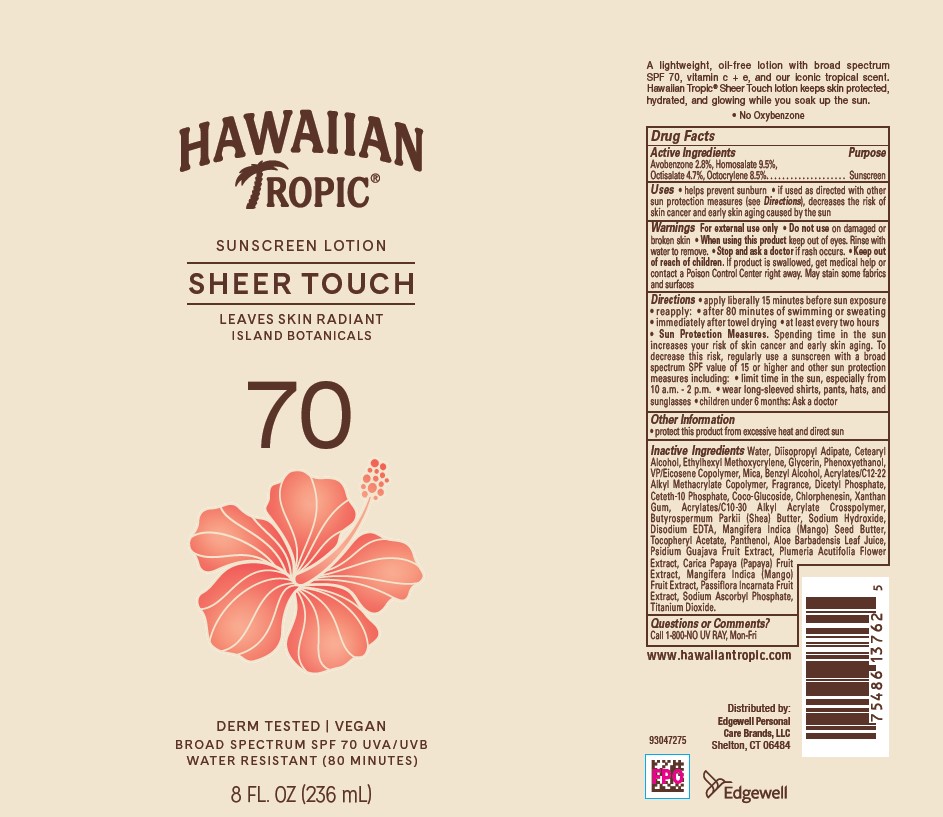 DRUG LABEL: HAWAIIAN TROPIC SUNSCREEN SHEER TOUCH SPF 70
NDC: 63354-386 | Form: LOTION
Manufacturer: Edgewell Personal Care Brands LLC
Category: otc | Type: HUMAN OTC DRUG LABEL
Date: 20251218

ACTIVE INGREDIENTS: OCTOCRYLENE 8.5 g/100 g; AVOBENZONE 2.8 g/100 g; OCTISALATE 4.7 g/100 g; HOMOSALATE 9.5 g/100 g
INACTIVE INGREDIENTS: DIHEXADECYL PHOSPHATE; COCO GLUCOSIDE; CHLORPHENESIN; XANTHAN GUM; SHEA BUTTER; SODIUM HYDROXIDE; EDETATE DISODIUM ANHYDROUS; MANGIFERA INDICA SEED; PANTHENOL; GUAVA; PLUMERIA RUBRA FLOWER; MANGO; DIISOPROPYL ADIPATE; EICOSYL POVIDONE; ACRYLIC ACID; WATER; CETETH-10 PHOSPHATE; GLYCERIN; BENZYL ALCOHOL; PAPAYA; CETOSTEARYL ALCOHOL; ETHYLHEXYL METHOXYCRYLENE; PHENOXYETHANOL; MICA; TITANIUM DIOXIDE; PASSIFLORA INCARNATA FRUIT; SODIUM ASCORBYL PHOSPHATE; ALPHA-TOCOPHEROL ACETATE; ALOE VERA LEAF

Active Ingredients

Avobenzone 2.8%, Homosalate 9.5%, Octisalate 4.7%, Octocrylene 8.5%.

Purpose

Sunscreen

Uses

• helps prevent sunburn • if used as directed with other sun protection measures (see Directions), decreases the risk of skin cancer and early skin aging caused by the sun

Warnings

For external use only.

May stain some fabrics and surfaces

When using this product

keep out of eyes. Rinse with water to remove.

Do not use

on damaged or broken skin

Stop and ask a doctor

if rash occurs

Keep out of reach of children.

If product is swallowed, get medical help or contact a Poison Control Center right away

Directions

• apply liberally 15 minutes before sun exposure • reapply: • after 80 minutes of swimming or sweating • immediately after towel drying • at least every two hours • Sun Protection Measures. Spending time in the sun increases your risk of skin cancer and early skin aging. To decrease this risk, regularly use a sunscreen with a broad spectrum SPF value of 15 or higher and other sun protection measures including: • limit time in the sun, especially from 10 a.m. - 2 p.m. • wear long-sleeved shirts, pants, hats, and sunglasses • children under 6 months: Ask a doctor

Other Information

• protect this product from excessive heat and direct sun

Inactive Ingredients

Water, Diisopropyl Adipate, Cetearyl Alcohol, Ethylhexyl Methoxycrylene, Glycerin, Phenoxyethanol, VP/Eicosene Copolymer, Mica, Benzyl Alcohol, Acrylates/C12-22 Alkyl Methacrylate Copolymer, Fragrance, Dicetyl Phosphate, Ceteth-10 Phosphate, Coco Glucoside, Chlorphenesin, Xanthan Gum, Acrylates/C10-30 Alkyl Acrylate Crosspolymer, Butyrospermum Parkii (Shea) Butter, Sodium Hydroxide, Disodium EDTA, Mangifera Indica (Mango) Seed Butter, Tocopheryl Acetate, Panthenol, Aloe Barbadensis Leaf Juice, Psidium Guajava Fruit Extract, Plumeria Acutifolia Flower Extract, Carica Papaya (Papaya) Fruit Extract, Mangifera Indica
(Mango) Fruit Extract, Passiflora Incarnata Fruit Extract, Sodium Ascorbyl Phosphate, Titanium Dioxide.

Questions or Comments?

Call 1-800-NO UV RAY, Mon-Fri

PRINCIPAL DISPLAY PANEL

HAWAIIAN

TROPIC

SUNSCREEN LOTION

SHEER TOUCH

LEAVES SKIN RADIANT

ISLAND BOTANICALS

70

DERM TESTED | VEGAN
BROAD SPECTRUM SPF 70 UVA/UVB
WATER RESISTANT (80 MINUTES)

8 FL. OZ (236 mL)